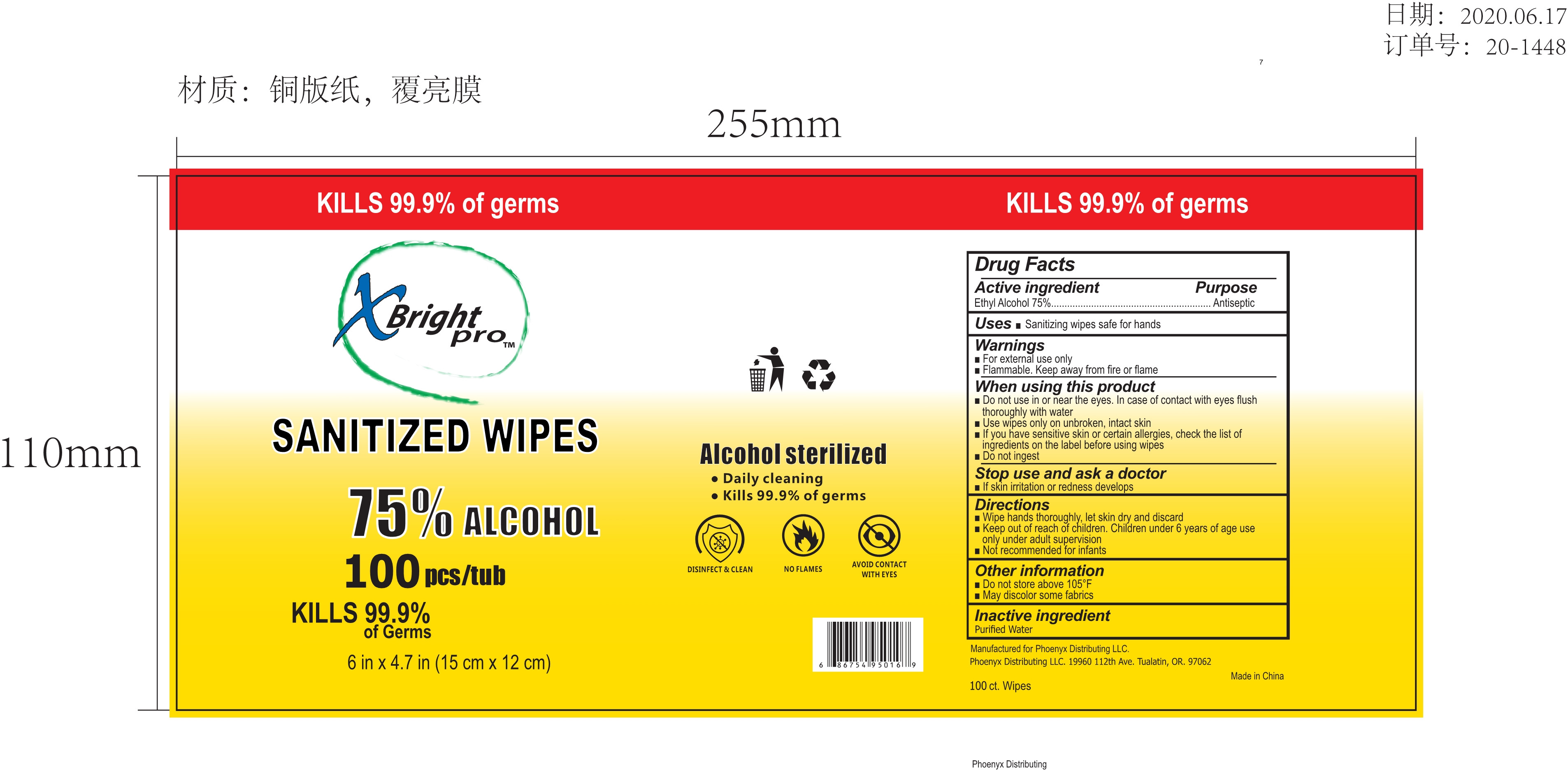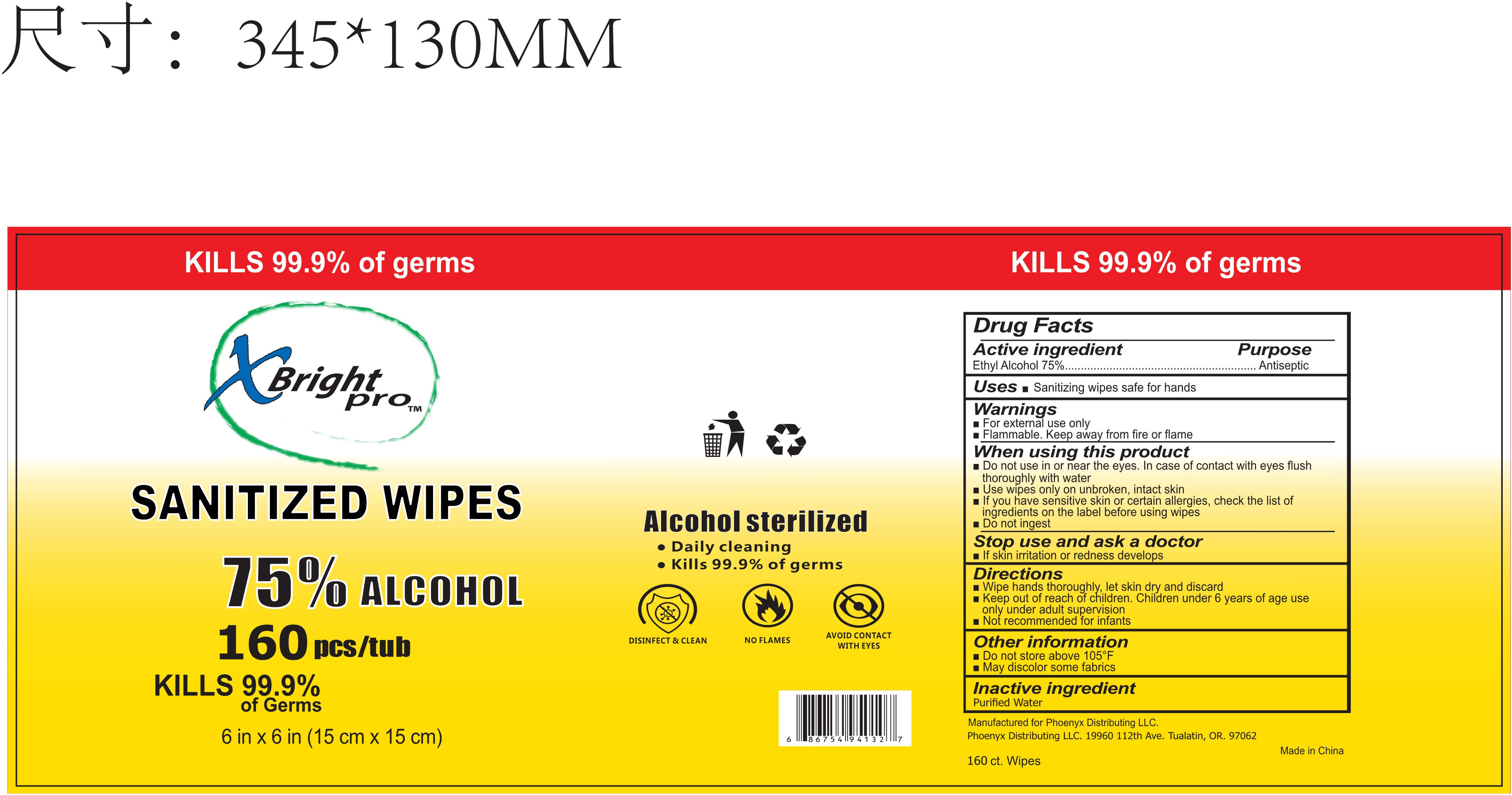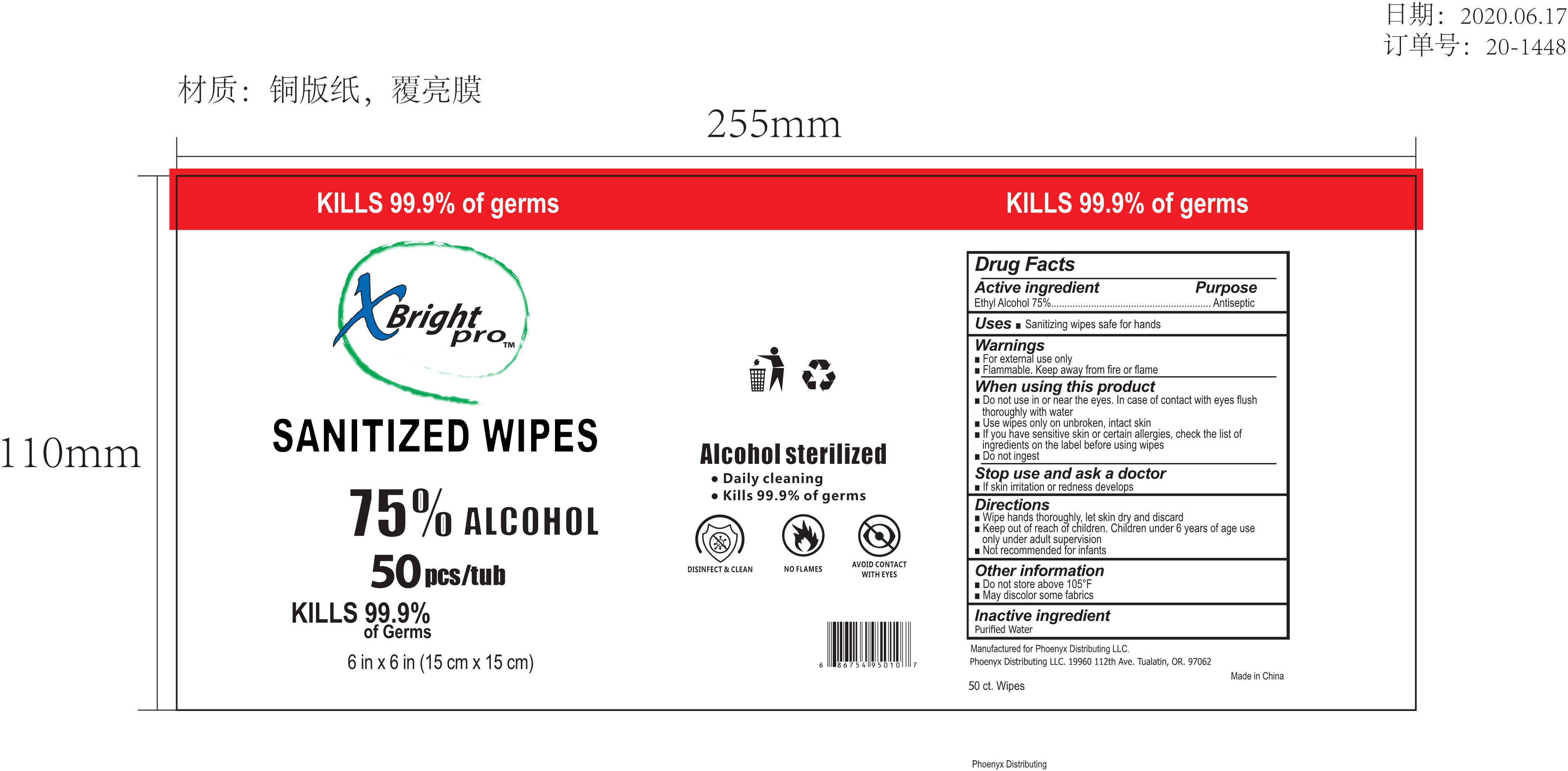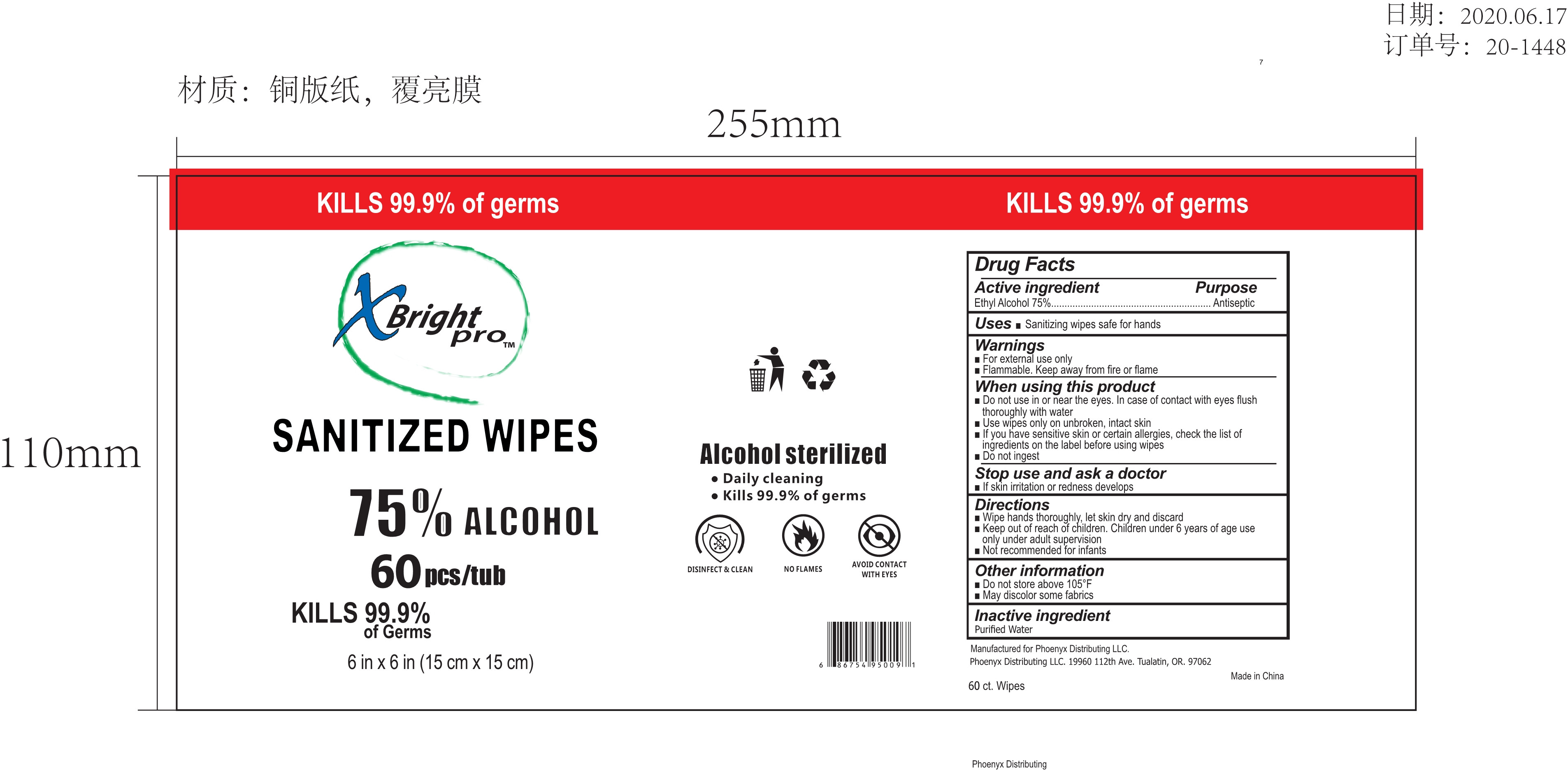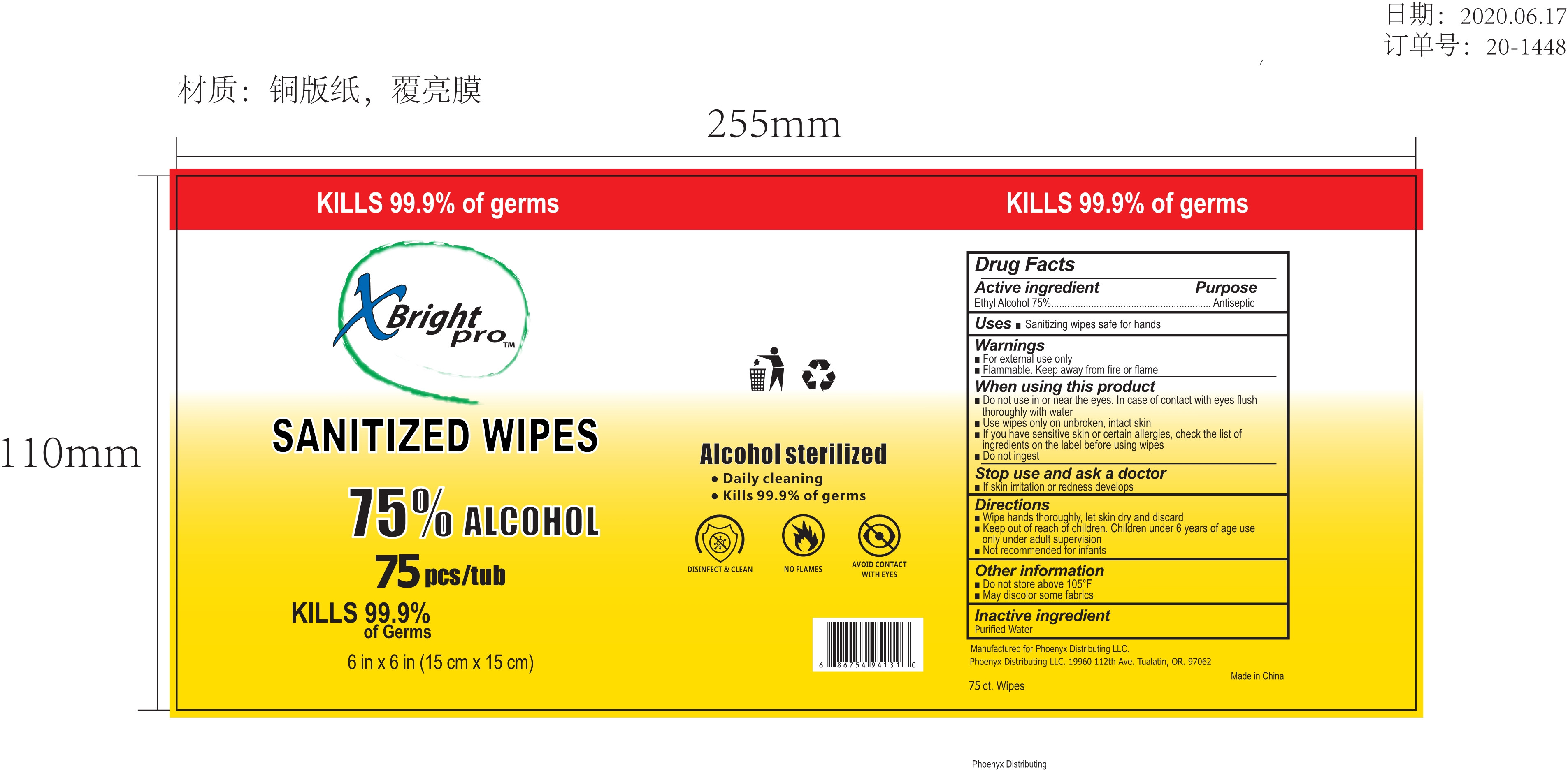 DRUG LABEL: SANITIZED WIPES
NDC: 79316-006 | Form: CLOTH
Manufacturer: PHOENYX DISTRIBUTING, LLC
Category: otc | Type: HUMAN OTC DRUG LABEL
Date: 20200624

ACTIVE INGREDIENTS: ALCOHOL 75 1/100 1
INACTIVE INGREDIENTS: WATER

Active Ingredient(s)

Ethly Alcohol 75% v/v. Purpose: Antiseptic

Purpose

Antiseptic, Hand Sanitizer

Use

Sanitizing wipes safe for hands

Warnings

Flammable away from fire or flame

- Do not use in or near the eyes. In case of contact with eyes flush thoroughly with water

When using this product

Do not use in or near the eyes. In case of contact with eyes flush thoroughly with water

Use wipes only on unbroken, intact skin

If you have sensitive skin or certain allergies, check the list of Ingredients on the label before using wipe.

Do not ingest

Stop use and ask a doctor

If skin irritation or redness develops

Keep out of reach of children. Children under 6 years of age use only under adult supervision

Not recommended for infants

Directions

  Wipe hands thoroughly, let skin dry and discard

Other information

- Do not store above 105FMay discolor some fabrics

Inactive ingredients

Purified Water